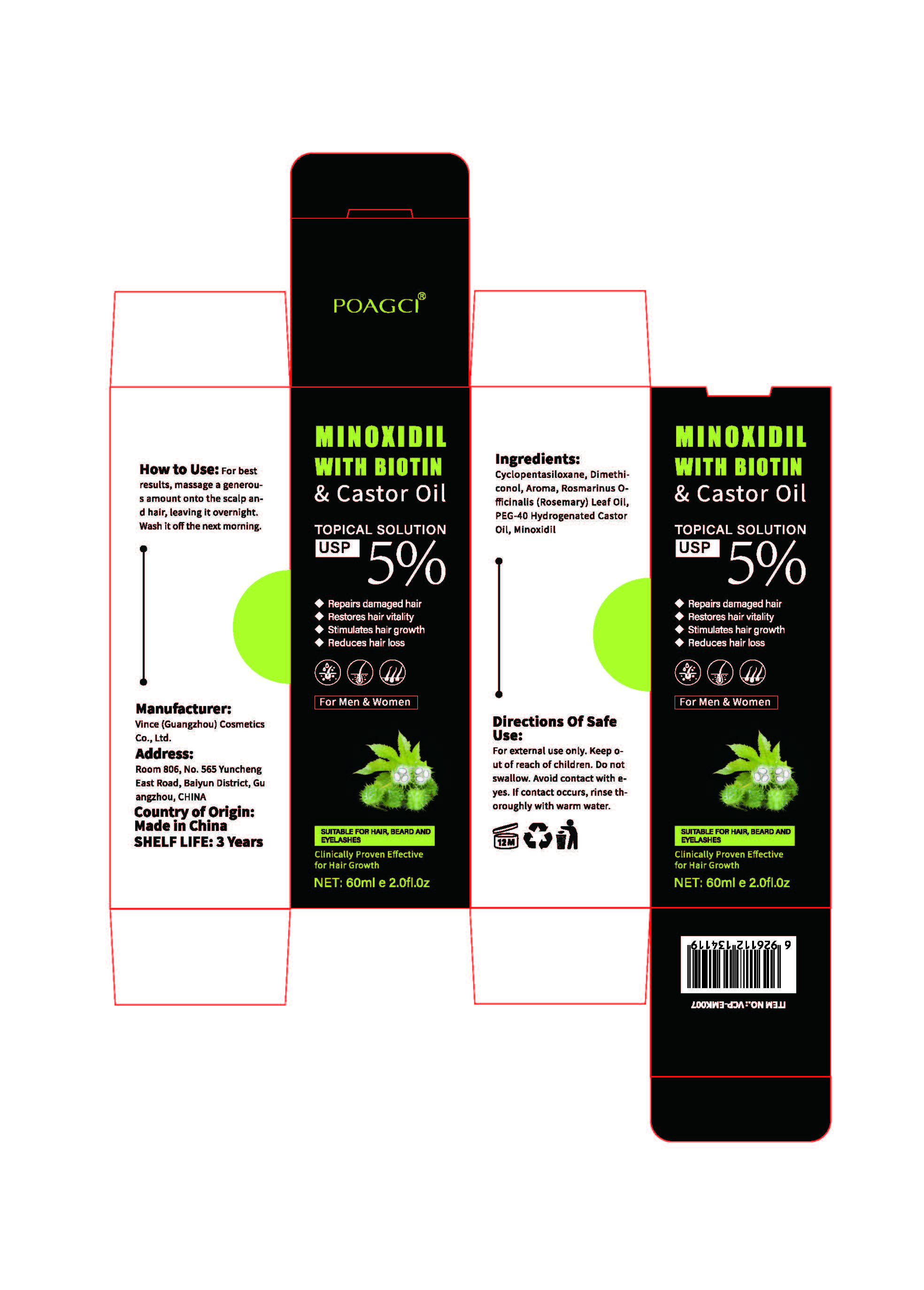 DRUG LABEL: Biotin Castor Essential Oil (Minoxidil 5%) VCP-EMK007
NDC: 84745-001 | Form: OIL
Manufacturer: Vince (Guangzhou) Cosmetics Co., Ltd.
Category: otc | Type: HUMAN OTC DRUG LABEL
Date: 20240917

ACTIVE INGREDIENTS: MINOXIDIL 30 mg/60 mL
INACTIVE INGREDIENTS: POLYOXYL 40 HYDROGENATED CASTOR OIL; ROSEMARY OIL

ACTIVE INGREDIENT

Minoxidil 0.05%

PURPOSE

Hair growth

INDICATIONS AND USAGE

Promotes Hair Growth

If used as directed with other hair growth products (see direction of use), promote hair growth for fuller, healthier and volumizing hair.

WARNINGS

For external use only.

Stop use and consult a doctor if rash occurs.

Do not used on damaged skin.

Keep out of reach of children.

If swallowed, get medical help or contact a Poison Control Center immediately.

When using this product, avoid contact with eyes. Rinse with water to remove.

DOSAGE AND ADMINISTRATION

Apply sufficient amount to your scalp and hair roots. Comb thoroughly.

INACTIVE INGREDIENT

POLYOXYL 40 HYDROGENATED CASTOR OIL 0.2%
ROSEMARY OIL 0.2%